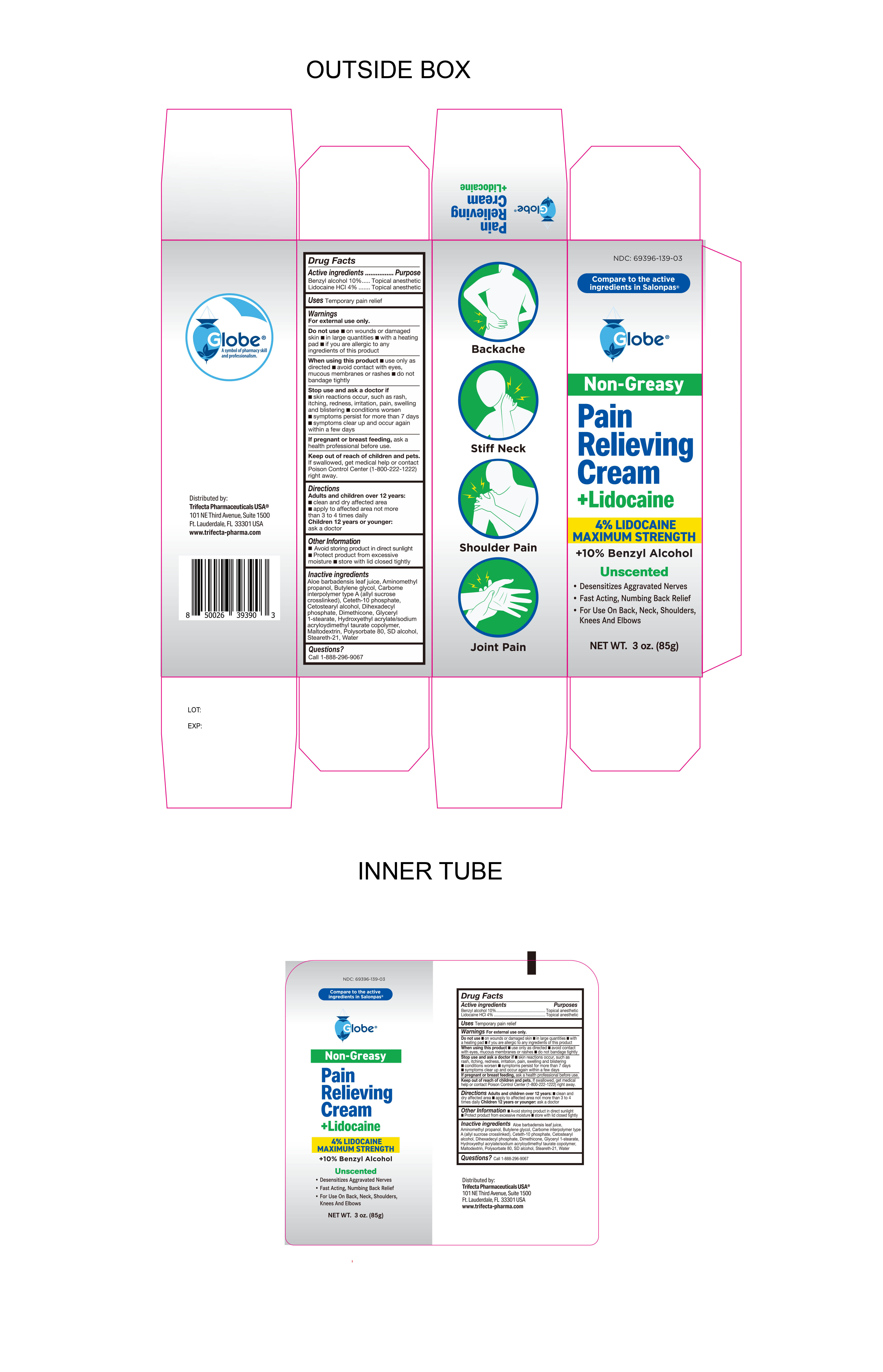 DRUG LABEL: Pain Relieving Cream  Lidocaine
NDC: 69396-139 | Form: CREAM
Manufacturer: Trifecta Pharmaceuticals USA LLC
Category: otc | Type: HUMAN OTC DRUG LABEL
Date: 20241231

ACTIVE INGREDIENTS: LIDOCAINE HYDROCHLORIDE 4 g/100 g; BENZYL ALCOHOL 10 g/100 g
INACTIVE INGREDIENTS: DIHEXADECYL PHOSPHATE; HYDROXYETHYL ACRYLATE/SODIUM ACRYLOYLDIMETHYL TAURATE COPOLYMER (45000 MPA.S AT 1%); WATER; CETOSTEARYL ALCOHOL; ALOE VERA LEAF; MALTODEXTRIN; CARBOMER INTERPOLYMER TYPE A (ALLYL SUCROSE CROSSLINKED); BUTYLENE GLYCOL; CETETH-10 PHOSPHATE; STEARETH-21; AMINOMETHYLPROPANOL; DIMETHICONE; GLYCERYL 1-STEARATE; POLYSORBATE 80; ALCOHOL

Globe Pain Relieving Cream+ Lidocaine

Active Ingredient

Lidocaine HCL 4%

Purpose

Topical Anasthetic

ACTIVE INGREDIENT

Benzyl Alcohol 10%

Purpose

Topical Anesthetic

Uses

Temporary Pain Relief

Do Not Use

- On wounds or damaged skin
- In large quantities
- With a heating pad
- if you are allergic to any ingredients of this product

When Using this Product

- Use only as direcgted
- Avoid contact with eyes, mucous membranes or rashes
- Do not bandage tightly

Warnings

For external Use Only

Do not use

- in eyes
- in large quantities
- over raw or blistered areas, or on deep puncture wounds, animal bites, or serious burns
- for more than one week unless directed by a doctor

If Pregnant or Breast Feeding

Ask a health professional before use

Keep out of reach of children

If swallowed, get medical help or contact a Poison Control Center (800-222-1222) right away

Directions

Adults and children over 12 years

- clean and dry affected area
- Apply to affected area not more than 3 to 4 times daily

Children 12 years or younger

- ask a doctor

Stop Use and Ask a Doctor If

- Skin reactions occur, such as rash, itching, redness, irritation, pain, swelling and blistering
- Conditions worsen
- Symptoms persist for more than 7 days
- Symptoms clear up and occur again within a few days

Other Information

- Avoid storing product in direct sunlight
- Protect product from excessive moisture
- Store with lid closed tightly

Inactive Ingredients

Aloe barbadensis leaf juice, aminomethyl propanol, Butylene glycol, carbome interpolymer type A (allyl sucrose crosslinked), Ceteth-10 phosphate, Cetostearyl alcohol, Dihexadecyl phosphate, Dimethicone, Glyceryl 1-stearate, Hydroxyethly acrylate/sodium acryloydimethyl taurate copolymer, maltodextrin, polysorbate 80, SD alcohol, Steareth-21, water

Distributed By

Trifecta Pharmaceuticals USA®

101 NE Third Avenue, Suite 1500

Ft. Lauderdale, FL. 33301 USA

www.trifecta-pharma.com

Questions

Call 1-888-296-9067